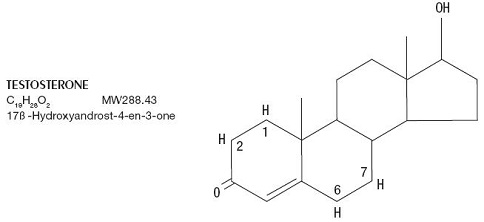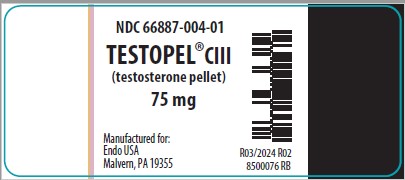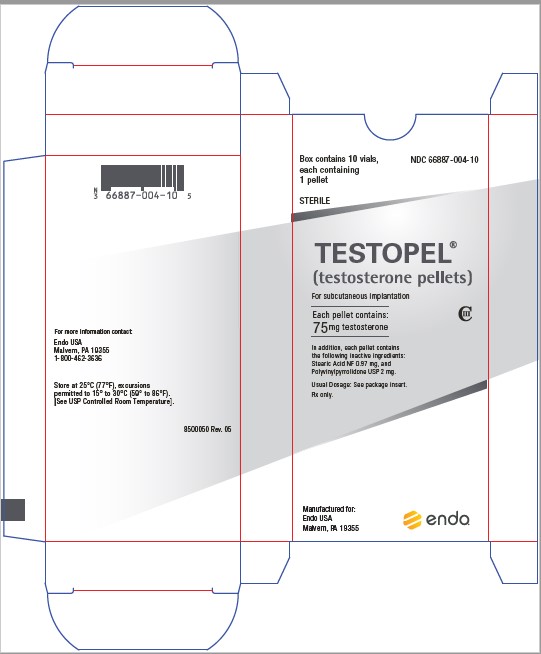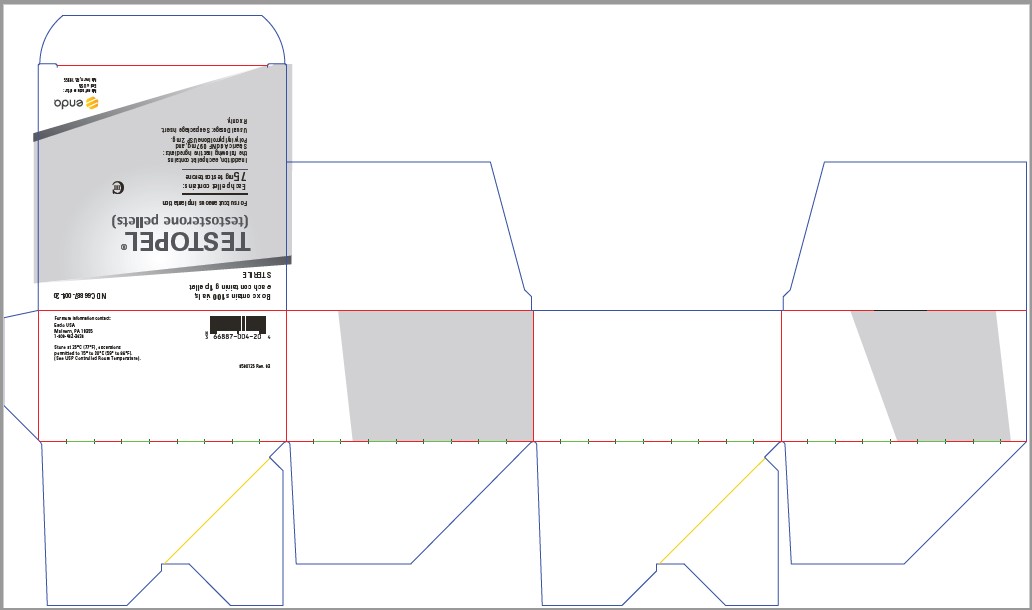 DRUG LABEL: Testopel
NDC: 66887-004 | Form: PELLET
Manufacturer: Endo USA, Inc.
Category: prescription | Type: HUMAN PRESCRIPTION DRUG LABEL
Date: 20250717
DEA Schedule: CIII

ACTIVE INGREDIENTS: TESTOSTERONE 75 mg/1 1

TESTOPEL®
(testosterone pellets)
CIII

DESCRIPTION

TESTOPEL® (testosterone pellets) are cylindrically shaped pellets 3.2mm (1/8 inch) in diameter and approximately 9mm in length. Each sterile pellet weighs approximately 78mg (75mg testosterone) and is ready for implantation.

Androgens are steroids that develop and maintain primary and secondary male sex characteristics. Testosterone is a member of this class.

Structural formula for testosterone follows:

INGREDIENTS

Each TESTOPEL® (testosterone pellets) for subcutaneous implantation contains 75mg testosterone. In addition each pellet contains the following inactive ingredients: stearic acid NF 0.97mg and polyvinylpyrrolidone USP 2mg.

TESTOPEL® (testosterone pellets) consist of crystalline testosterone. When implanted subcutaneously, the pellets slowly release the hormone for a long acting androgenic effect.

CLINICAL PHARMACOLOGY

Endogenous androgens are responsible for the normal growth and development of the male sex organs and for maintenance of secondary sex characteristics. These effects include the growth and maturation of prostate, seminal vesicles, penis and scrotum; the development of male hair distribution such as beard, pubic, chest and axillary hair, laryngeal enlargements, vocal cord thickening, alterations in body musculature and fat distribution. Drugs in this class can also cause retention of nitrogen, sodium, potassium, phosphorus, and decreased urinary excretion of calcium.

Androgens have been reported to increase protein anabolism and decrease protein catabolism.

Nitrogen balance is improved only when there is sufficient intake of calories and protein.

Androgens are responsible for the growth spurt of adolescence and for the eventual termination of linear growth which is brought about by the fusion of the epiphyseal growth centers. In children, exogenous androgens accelerate linear growth rates, but may cause a disproportionate advancement in bone maturation. Use over long periods may result in fusion of the epiphyseal growth centers and termination of growth process. Androgens have been reported to stimulate the production of red blood cells by enhancing the production of erythropoietic stimulating factor.

During exogenous administration of androgens, endogenous testosterone release is inhibited through feedback inhibition of pituitary luteinizing hormone (LH). At large doses of exogenous androgens, spermatogenesis may also be suppressed through feedback inhibition of pituitary follicle stimulating hormone (FSH).

There is a lack of substantial evidence that androgens are effective in fractures, surgery, convalescence, and functional uterine bleeding.

PHARMACOKINETICS

Testosterone in plasma is 98 percent bound to a specific testosterone-estradiol binding globulin, and about 2 percent is free. Generally, the amount of this sex-hormone binding globulin in the plasma will determine the distribution of testosterone between the free and bound forms, and the free testosterone concentration will determine its half-life.

About 90 percent of a dose of testosterone is excreted as glucuronic and sulfuric acid conjugates of testosterone and its metabolites; about 6 percent of a dose is excreted in feces, mostly in the unconjugated form. Inactivation of testosterone occurs primarily in the liver. Testosterone is metabolized to various 17-keto steroids through two different pathways. There are considerable variations of the half-life as reported in the literature, ranging from 10-100 minutes.

In many tissues the activity of testosterone appears to depend on reduction to dihydrotestosterone, which binds to cytosol receptor proteins. The steroid-receptor complex is transported to the nucleus where it initiates transcription events and cellular changes related to androgen action.

INDICATIONS AND USAGE

MALES

Androgens are indicated for replacement therapy in conditions associated with a deficiency or absence of endogenous testosterone.

a. Primary hypogonadism (congenital or acquired) - testicular failure due to cryptorchidism, bilateral torsion, orchitis, vanishing testes syndrome; or orchiectomy.

b. Hypogonadotropic hypogonadism (congenital or acquired) - gonadotropic LHRH deficiency, or pituitary - hypothalamic injury from tumors, trauma or radiation.

If the above conditions occur prior to puberty, androgen replacement therapy will be needed during the adolescent years for development of secondary sex characteristics. Prolonged androgen treatment will be required to maintain sexual characteristics in these and other males who develop testosterone deficiency after puberty.

Safety and efficacy of TESTOPEL® (testosterone pellets) in men with “age-related hypogonadism” (also referred to as “late-onset hypogonadism”) have not been established.

c. Androgens may be used to stimulate puberty in carefully selected males with clearly delayed puberty. These patients usually have a familial pattern of delayed puberty that is not secondary to a pathological disorder; puberty is expected to occur spontaneously at a relatively late date. Brief treatment with conservative doses may occasionally be justified in these patients if they do not respond to psychological support. The potential adverse effect on bone maturation should be discussed with the patient and parents prior to androgen administration. An x-ray of the hand and wrist to determine bone age should be taken every 6 months to assess the effect of treatment on epiphyseal centers (see WARNINGS).

CONTRAINDICATIONS

Androgens are contraindicated in men with carcinomas of the breast or with known or suspected carcinomas of the prostate. If administered to pregnant women, androgens cause virilization of the external genitalia of the female fetus. The virilization includes clitoromegaly, abnormal vaginal development, and fusion of genital folds to form a scrotal-like structure. The degree of masculinization is related to the amount of drug given and the age of the fetus, and is most likely to occur in the female fetus when the drugs are given in the first trimester. If the patient becomes pregnant while taking these drugs she should be apprised of the potential hazard to the fetus.

WARNINGS

In patients with breast cancer, androgen therapy may cause hypercalcemia by stimulating osteolysis. In this case, the drug should be discontinued.

Prolonged use of high doses of androgens has been associated with the development of peliosis hepatis and hepatic neoplasms including hepatocellular carcinoma (see PRECAUTIONS - Carcinogenesis, Mutagenesis, Impairment of Fertility). Peliosis hepatis can be a life-threatening or fatal complication.

Men treated with androgens may be at an increased risk for the development of prostatic hypertrophy and prostatic carcinoma.

There have been postmarketing reports of venous thromboembolic events, including deep vein thrombosis (DVT) and pulmonary embolism (PE), in patients using testosterone products, such as TESTOPEL® (testosterone pellets). Evaluate patients who report symptoms of pain, edema, warmth and erythema in the lower extremity for DVT and those who present with acute shortness of breath for PE. If a venous thromboembolic event is suspected, discontinue treatment with TESTOPEL® (testosterone pellets) and initiate appropriate workup and management (see ADVERSE REACTIONS).

Long term clinical safety trials have not been conducted to assess the cardiovascular outcomes of testosterone replacement therapy in men. To date, epidemiologic studies and randomized controlled trials have been inconclusive for determining the risk of major adverse cardiovascular events (MACE), such as non-fatal myocardial infarction, non-fatal stroke, and cardiovascular death, with the use of testosterone compared to non-use. Some studies, but not all, have reported an increased risk of MACE in association with use of testosterone replacement therapy in men. Patients should be informed of this possible risk when deciding whether to use or to continue to use TESTOPEL® (testosterone pellets).

Testosterone can increase blood pressure which can increase cardiovascular (CV) risk over time. Monitor blood pressure periodically in men using testosterone products, especially in men with hypertension. Testosterone products are not recommended for use in patients with uncontrolled hypertension.

Testosterone has been subject to abuse, typically at doses higher than recommended for the approved indication and in combination with other anabolic androgenic steroids. Anabolic androgenic steroid abuse can lead to serious cardiovascular and psychiatric adverse reactions (see DRUG ABUSE AND DEPENDENCE).

If testosterone abuse is suspected, check serum testosterone concentrations to ensure they are within therapeutic range. However, testosterone levels may be in the normal or subnormal range in men abusing synthetic testosterone derivatives. Counsel patients concerning the serious adverse reactions associated with abuse of testosterone and anabolic androgenic steroids. Conversely, consider the possibility of testosterone and anabolic androgenic steroid abuse in suspected patients who present with serious cardiovascular or psychiatric adverse events.

Edema with or without congestive heart failure may be a serious complication in patients with preexisting cardiac, renal, or hepatic disease. In addition to discontinuation of the drug, diuretic therapy may be required.

Gynecomastia frequently develops in patients and occasionally persists in patients being treated for hypogonadism.

Androgen therapy should be used cautiously in healthy males with delayed puberty. The effect on bone maturation should be monitored by assessing bone age of the wrist and hand every 6 months. In children, androgen treatment may accelerate bone maturation without producing compensatory gain in linear growth. This adverse effect may result in compromised adult stature. The younger the child the greater the risk of compromising final mature height.

Post-marketing cases associate TESTOPEL® pellet(s) insertion with implant site infection (cellulitis and abscess), and/or pellet extrusion at or near the implantation site. Infection and extrusion may occur concurrently or separately. Reported signs and symptoms of infection and/or extrusion at the implant site included induration, inflammation, fibrosis, bleeding, bruising, wound drainage, pain, itching, and pellet extrusion. Although cases of infection and/or extrusion may occur at any time, most reported cases occurred within the first month after TESTOPEL® implantation. Infection and/or extrusion may require further treatment (see ADVERSE REACTIONS).

This drug has not been shown to be safe and effective for the enhancement of athletic performance. Because of the potential risk for serious adverse health effects, this drug should not be used for such purpose.

PRECAUTIONS

GENERAL

Pellet implantation is much less flexible for dosage adjustment than is oral administration of or intramuscular injections of oil solutions or aqueous suspensions. Therefore, great care should be used when estimating the amount of testosterone needed.

In the face of complications where the effects of testosterone should be discontinued, the pellets would have to be removed.

INFORMATION FOR THE PATIENT

The physician should instruct patients to report any of the following side effects of androgens:

Adult or adolescent males: Too frequent or persistent erections of the penis. Any nausea, vomiting, changes in skin color, ankle swelling.

Implantation site infection and/or pellet extrusion can occur and may be associated with implant site induration, inflammation, fibrosis, bleeding, bruising, wound drainage, pain, itching, and pellet extrusion. (see WARNINGS and ADVERSE REACTIONS).

Any male adolescent patient receiving androgens for delayed puberty should have bone development checked every 6 months.

LABORATORY TESTS

1. Because of the hepatotoxicity associated with the use of 17-alpha-alkylated androgens, liver function tests should be obtained periodically.
2. Periodic (every 6 months) x-ray examinations of the bone age should be made during treatment of prepubertal males to determine the rate of bone maturation and the effects of androgen therapy on the epiphyseal centers.
3. Hemoglobin and hematocrit should be checked periodically for polycythemia in patients who are receiving high doses of androgens.

DRUG INTERACTIONS

1. Anticoagulants. C-17 substituted derivatives of testosterone, such as methandrostenolone have been reported to decrease the anticoagulant requirements of patients receiving oral anticoagulants. Patients receiving oral anticoagulant therapy require close monitoring, especially when androgens are started or stopped.
2. Oxyphenbutazone. Concurrent administration of oxyphenbutazone and androgens may result in elevated serum levels of oxyphenbutazone.
3. Insulin. In diabetic patients the metabolic effects of androgens may decrease blood glucose and insulin requirements.

DRUG/LABORATORY TEST INTERFERENCES

Androgens may decrease levels of thyroxine-binding globulin, resulting in decreased total T4 serum levels and increased resin uptake of T3 and T4. Free thyroid hormone levels remain unchanged, however, and there is no clinical evidence of thyroid dysfunction.

CARCINOGENESIS, MUTAGENESIS, IMPAIRMENT OF FERTILITY

Animal Data. Testosterone has been tested by subcutaneous injection and implantation in mice and rats. The implant induced cervical-uterine tumors in mice, which metastasized in some cases. There is suggestive evidence that injection of testosterone into some strains of female mice increases their susceptibility to hepatoma. Testosterone is also known to increase the number of tumors and decrease the degree of differentiation of chemically induced carcinomas of liver in rats.

Human Data. There are rare reports of hepatocellular carcinoma in patients receiving long-term therapy with androgens in high doses. Withdrawal of the drugs did not lead to regression of the tumors in all cases.

Geriatric patients treated with androgens may be at an increased risk for the development of prostatic hypertrophy and prostatic carcinoma.

PREGNANCY

Teratogenic Effects. Pregnancy Category X (see CONTRAINDICATIONS).

NURSING MOTHERS

It is not known whether androgens are excreted in human milk. Because many drugs are excreted in human milk and because of the potential for serious adverse reactions in nursing infants from androgens, a decision should be made whether to discontinue nursing or to discontinue the drug, taking into account the importance of the drug to the mother.

PEDIATRIC USE

Androgen therapy should be used very cautiously in children and only by specialists who are aware of the adverse effects on bone maturation. Skeletal maturation must be monitored every 6 months by an x-ray of the hand and wrist (see INDICATIONS AND USAGE and WARNINGS).

ADVERSE REACTIONS

The following adverse reactions have been identified during post-approval use of testosterone replacement therapy, including TESTOPEL®. Because these reactions are reported voluntarily from a population of uncertain size, it is not always possible to reliably estimate their frequency or establish a causal relationship to drug exposure.

Implantation Site Infection and Pellet Extrusion: (see WARNINGS)

Endocrine and Urogenital, Male. Gynecomastia and excessive frequency and duration of penile erections. Oligospermia may occur at high dosages (see CLINICAL PHARMACOLOGY).

Skin and Appendages. Hirsutism, male pattern of baldness, and acne.

Cardiovascular Disorders. Myocardial infarction, stroke.

Fluid and Electrolyte Disturbances. Retention of sodium, chloride, water, potassium, calcium and inorganic phosphates.

Gastrointestinal. Nausea, cholestatic jaundice, alterations in liver function tests, rarely hepatocellular neoplasms and peliosis hepatis (see WARNINGS).

Hematologic. Suppression of clotting factors II, V, VII, and X, bleeding in patients on concomitant anticoagulant therapy, and polycythemia.

Nervous System. Increased or decreased libido, headache, anxiety, depression, and generalized paresthesia.

Metabolic. Increased serum cholesterol.

Vascular Disorders: Venous thromboembolism (see WARNINGS).

Miscellaneous. Rarely anaphylactoid reactions.

DRUG ABUSE AND DEPENDENCE

Controlled Substance

TESTOPEL® contains testosterone, a Schedule III controlled substance in the Controlled Substances Act.

Abuse

Drug abuse is intentional non-therapeutic use of a drug, even once, for its rewarding psychological and physiological effects. Abuse and misuse of testosterone are seen in male and female adults and adolescents. Testosterone, often in combination with other anabolic androgenic steroids (AAS), and not obtained by prescription through a pharmacy, may be abused by athletes and bodybuilders. There have been reports of misuse of men taking higher doses of legally obtained testosterone than prescribed and continuing testosterone despite adverse events or against medical advice.

Abuse-Related Adverse Reactions

Serious adverse reactions have been reported in individuals who abuse anabolic androgenic steroids, and include cardiac arrest, myocardial infarction, hypertrophic cardiomyopathy, congestive heart failure, cerebrovascular accident, hepatotoxicity, and serious psychiatric manifestations, including major depression, mania, paranoia, psychosis, delusions, hallucinations, hostility and aggression.

The following adverse reactions have also been reported in men: transient ischemic attacks, convulsions, hypomania, irritability, dyslipidemias, testicular atrophy, subfertility, and infertility.

The following additional adverse reactions have been reported in women: hirsutism, virilization, deepening of voice, clitoral enlargement, breast atrophy, male-pattern baldness, and menstrual irregularities.

The following adverse reactions have been reported in male and female adolescents: premature closure of bony epiphyses with termination of growth, and precocious puberty.

Because these reactions are reported voluntarily from a population of uncertain size and may include abuse of other agents, it is not always possible to reliably estimate their frequency or establish a causal relationship to drug exposure.

Dependence

Behaviors Associated with Addiction

Continued abuse of testosterone and other anabolic steroids, leading to addiction is characterized by the following behaviors:

- Taking greater dosages than prescribed
- Continued drug use despite medical and social problems due to drug use
- Spending significant time to obtain the drug when supplies of the drug are interrupted
- Giving a higher priority to drug use than other obligations
- Having difficulty in discontinuing the drug despite desires and attempts to do so
- Experiencing withdrawal symptoms upon abrupt discontinuation of use

Physical dependence is characterized by withdrawal symptoms after abrupt drug discontinuation or a significant dose reduction of a drug. Individuals taking supratherapeutic doses of testosterone may experience withdrawal symptoms lasting for weeks or months which include depressed mood, major depression, fatigue, craving, restlessness, irritability, anorexia, insomnia, decreased libido and hypogonadotropic hypogonadism.

Drug dependence in individuals using approved doses of testosterone for approved indications has not been documented.

OVERDOSAGE

There have been no reports of acute overdosage with the androgens.

DOSAGE AND ADMINISTRATION

Prior to initiating, TESTOPEL® (testosterone pellets) confirm the diagnosis of hypogonadism by ensuring that serum testosterone concentrations have been measured in the morning on at least two separate days and that these serum testosterone concentrations are below the normal range.

The suggested dosage for androgens varies depending on the age, and diagnosis of the individual patient. Dosage is adjusted according to the patient’s response and the appearance of adverse reactions. The dosage guideline for the testosterone pellets for replacement therapy in androgen-deficient males is 150mg to 450mg subcutaneously every 3 to 6 months. Various dosage regimens have been used to induce pubertal changes in hypogonadal males; some experts have advocated lower doses initially, gradually increasing the dose as puberty progresses, with or without a decrease in maintenance levels. Other experts emphasize that higher dosages are needed to induce pubertal changes and lower dosages can be used for maintenance after puberty. The chronological and skeletal ages must be taken into consideration, both in determining the initial dose and in adjusting the dose.

Dosages in delayed puberty generally are in the lower range of that listed above and, for a limited duration, for example 4 to 6 months.

The number of pellets to be implanted depends upon the minimal daily requirements of testosterone propionate determined by a gradual reduction of the amount administered parenterally. The usual dosage is as follows: implant two 75mg pellets for each 25mg testosterone propionate required weekly. Thus when a patient requires injections of 75mg per week, it is usually necessary to implant 450mg (6 pellets). With injections of 50mg per week, implantation of 300mg (4 pellets) may suffice for approximately three months. With lower requirements by injection, correspondingly lower amounts may be implanted. It has been found that approximately one-third of the material is absorbed in the first month, one-fourth in the second month and one-sixth in the third month. Adequate effect of the pellets ordinarily continues for three to four months, sometimes as long as six months.

HOW SUPPLIED

Testosterone pellets each containing 75mg testosterone. One pellet per vial in boxes of 10 (NDC: 66887-004-10) and 100 (NDC: 66887-004-20). Store at 25°C (77°F), excursions permitted to 15° to 30°C (59° to 86°F). [See USP Controlled Room Temperature].

Rx Only
Manufactured for:
Endo USA
Malvern, PA 19355

© 2025 Endo, Inc. or one of its affiliates.

Revised 07/2025

Principal Display Panel – Vial Label

PACKAGE LABEL

Principal Display Panel – Box of 10 Vials

PACKAGE LABEL

Principal Display Panel – Box of 100 Vials